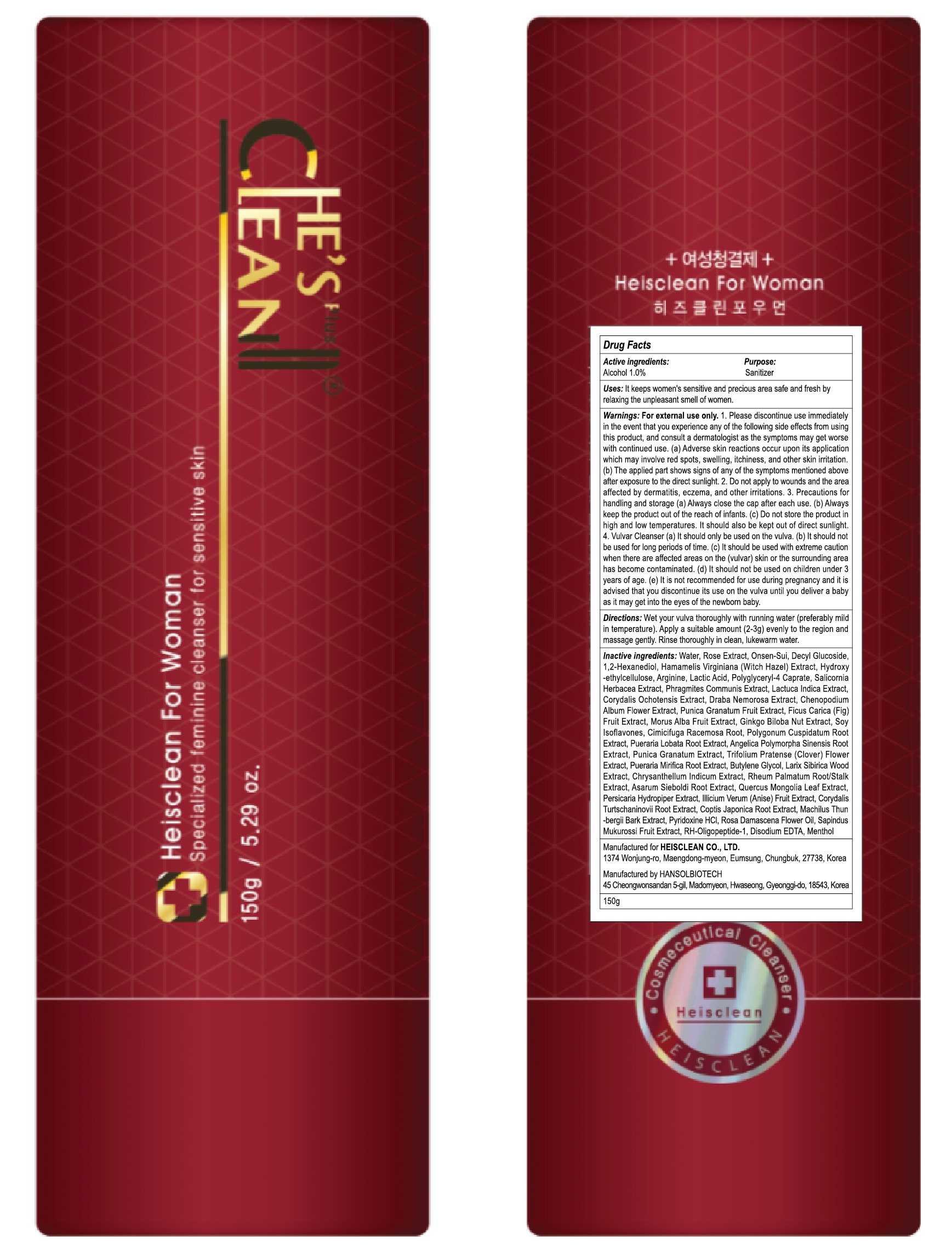 DRUG LABEL: HEISCLEAN FOR WOMAN
NDC: 42979-160 | Form: GEL
Manufacturer: HEISCLEAN.CO.,LTD
Category: otc | Type: HUMAN OTC DRUG LABEL
Date: 20171208

ACTIVE INGREDIENTS: Alcohol 2 g/200 g
INACTIVE INGREDIENTS: Water; Witch Hazel

ACTIVE INGREDIENT

Active Ingredient: Alcohol 1.0%

INACTIVE INGREDIENT

Inactive Ingredients: Water, Rose Extract, Onsen-Sui, Decyl Glucoside, 1,2-Hexanediol, Hamamelis Virginiana (Witch Hazel) Extract, Hydroxyethylcellulose, Arginine, Lactic Acid, Polyglyceryl-4 Caprate, Salicornia Herbacea Extract, Phragmites Communis Extract, Lactuca Indica Extract, Corydalis Ochotensis Extract, Draba Nemorosa Extract, Chenopodium Album Flower Extract, Punica Granatum Fruit Extract, Ficus Carica (Fig) Fruit Extract, Morus Alba Fruit Extract, Ginkgo Biloba Nut Extract, Soy Isoflavones, Cimicifuga Racemosa Root, Polygonum Cuspidatum Root Extract, Pueraria Lobata Root Extract, Angelica Polymorpha Sinensis Root Extract, Punica Granatum Extract, Trifolium Pratense (Clover) Flower Extract, Pueraria Mirifica Root Extract, Butylene Glycol, Larix Sibirica Wood Extract, Chrysanthellum Indicum Extract, Rheum Palmatum Root/Stalk Extract, Asarum Sieboldi Root Extract, Quercus Mongolia Leaf Extract, Persicaria Hydropiper Extract, Illicium Verum (Anise) Fruit Extract, Corydalis Turtschaninovii Root Extract, Coptis Japonica Root Extract, Machilus Thunbergii Bark Extract, Pyridoxine HCl, Rosa Damascena Flower Oil, Sapindus Mukurossi Fruit Extract, RH-Oligopeptide-1, Disodium EDTA, Menthol

PURPOSE

Purpose: Sanitizer

WARNINGS

For external use only

1. Please discontinue use immediately in the event that you experience any of the following side effects from using this product, and consult a dermatologist as the symptoms may get worse with continued use. (a) Adverse skin reactions occur upon its application which may involve red spots, swelling, itchiness, and other skin irritation. (b) The applied part shows signs of any of the symptoms mentioned above after exposure to the direct sunlight.

2. Do not apply to wounds and the area affected by dermatitis, eczema, and other irritations.

3. Precautions for handling and storage (a) Always close the cap after each use. (b) Always keep the product out of the reach of infants. (c) Do not store the product in high and low temperatures. It should also be kept out of direct sunlight.

4. Vulvar Cleanser (a) It should only be used on the vulva. (b) It should not be used for long periods of time. (c) It should be used with extreme caution when there are affected areas on the (vulvar) skin or the surrounding area has become contaminated. (d) It should not be used on children under 3 years of age. (e) It is not recommended for use during pregnancy and it is advised that you discontinue its use on the vulva until you deliver a baby as it may get into the eyes of the newborn baby.

KEEP OUT OF REACH OF CHILDREN

Always keep the product out of the reach of infants.

Uses

It keeps women's sensitive and precious area safe and fresh by relaxing the unpleasant smell of women.

Directions

Wet your vulva thoroughly with running water (preferably mild in temperature). Apply a suitable amount (2-3g) evenly to the region and massage gently. Rinse thoroughly in clean, lukewarm water.